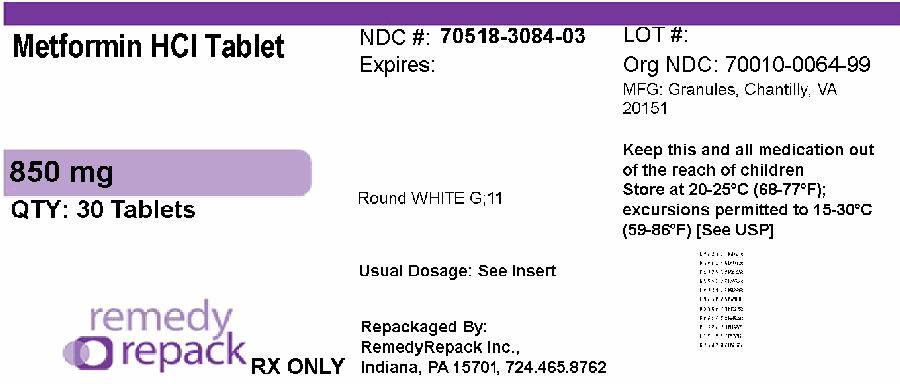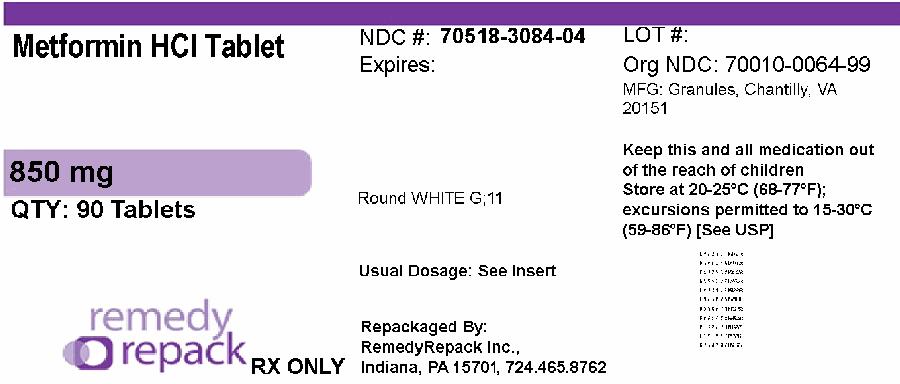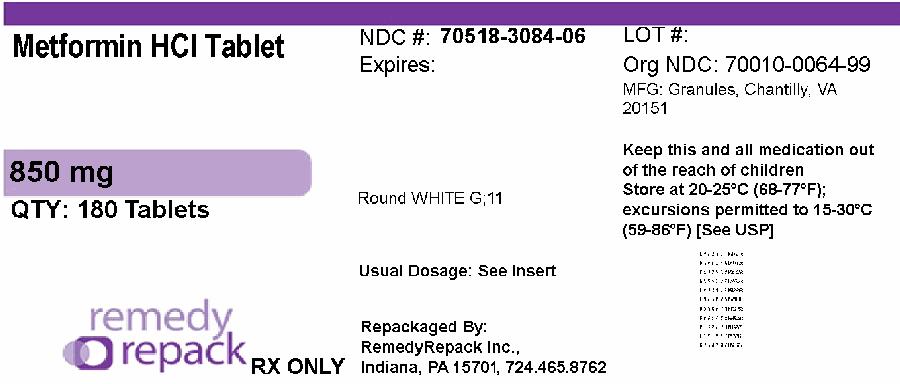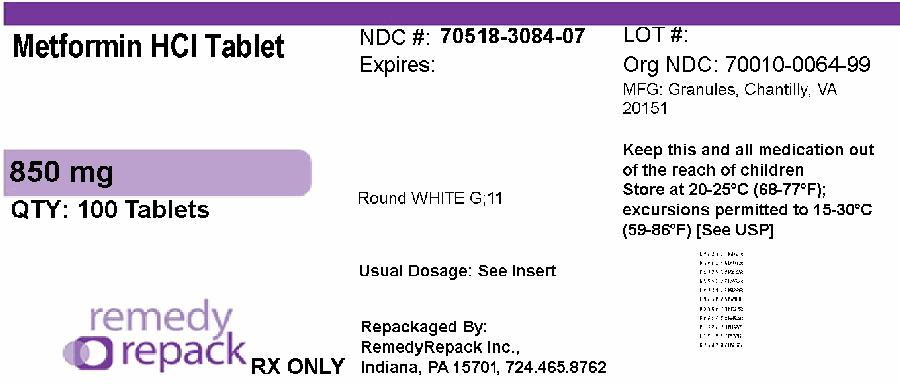 DRUG LABEL: Metformin Hydrochloride
NDC: 70518-3084 | Form: TABLET
Manufacturer: REMEDYREPACK INC.
Category: prescription | Type: HUMAN PRESCRIPTION DRUG LABEL
Date: 20260227

ACTIVE INGREDIENTS: METFORMIN HYDROCHLORIDE 850 mg/1 1
INACTIVE INGREDIENTS: MAGNESIUM STEARATE; BLACKBERRY; POVIDONE K30; POVIDONE K90; STARCH, CORN; TITANIUM DIOXIDE; HYPROMELLOSE 2910 (6 MPA.S); POLYETHYLENE GLYCOL 400

HIGHLIGHTS OF PRESCRIBING INFORMATION

These highlights do not include all the information needed to use METFORMIN HYDROCHLORIDE TABLETS safely and effectively. See full prescribing information for METFORMIN HYDROCHLORIDE TABLETS.
METFORMIN HYDROCHLORIDE tablets, for oral use
Initial U.S. Approval: 1995

BOXED WARNING

WARNING: LACTIC ACIDOSIS
See full prescribing information for complete boxed warning.

- Postmarketing cases of metformin-associated lactic acidosis have resulted in death, hypothermia, hypotension, and resistant bradyarrhythmias. Symptoms included malaise, myalgias, respiratory distress, somnolence, and abdominal pain. Laboratory abnormalities included elevated blood lactate levels, anion gap acidosis, increased lactate/pyruvate ratio; and metformin plasma levels generally >5 mcg/mL. (5.1)
- Risk factors include renal impairment, concomitant use of certain drugs, age >65 years old, radiological studies with contrast, surgery and other procedures, hypoxic states, excessive alcohol intake, and hepatic impairment. Steps to reduce the risk of and manage metformin associated lactic acidosis in these high risk groups are provided in the Full Prescribing Information. (5.1)
- If lactic acidosis is suspected, discontinue metformin hydrochloride tablets and institute general supportive measures in a hospital setting. Prompt hemodialysis is recommended. (5.1)

1 INDICATIONS & USAGE

Metformin hydrochloride tablets are biguanide indicated as an adjunct to diet and exercise to improve glycemic control in adults and pediatric patients 10 years of age and older with type 2 diabetes mellitus. (1)

2 DOSAGE & ADMINISTRATION

Adult Dosage for metformin hydrochloride tablets:

- Starting dose: 500 mg orally twice a day or 850 mg once a day, with meals (2.1)
- Increase the dose in increments of 500 mg weekly or 850 mg every 2 weeks, up to a maximum dose of 2550 mg per day, given in divided doses (2.1)
- Doses above 2000 mg may be better tolerated given 3 times a day with meals (2.1)

Pediatric Dosage for metformin hydrochloride tablets:

- Starting dose: 500 mg orally twice a day, with meals (2.2)
- Increase dosage in increments of 500 mg weekly up to a maximum of 2000 mg per day, given in divided doses twice daily (2.2)

Renal Impairment:

- Prior to initiation, assess renal function with estimated glomerular filtration rate (eGFR) (2.3)
- Do not use in patients with eGFR below 30 mL/minute/1.73 m^2(2.3)
- Initiation is not recommended in patients with eGFR between 30 to 45 mL/minute/1.73 m^2(2.3)
- Assess risk/benefit of continuing if eGFR falls below 45 mL/minute/1.73 m^2(2.3)
- Discontinue if eGFR falls below 30 mL/minute/1.73 m^2(2.3)

3 DOSAGE FORMS & STRENGTHS

- Metformin Hydrochloride Tablets: 850 mg

4 CONTRAINDICATIONS

- Severe renal impairment (eGFR below 30 mL/min/1.73 m^2) (4, 5.1)
- Hypersensitivity to metformin (4)
- Acute or chronic metabolic acidosis, including diabetic ketoacidosis, with or without coma. (4)

5 WARNINGS AND PRECAUTIONS

- Lactic Acidosis:See boxed warning. (5.1)
- Vitamin B 12 Deficiency:Metformin may lower vitamin B12 levels. Measure hematological parameters annually and vitamin B12 at 2 to 3 year intervals and manage any abnormalities. (5.2)
- Hypoglycemia with Concomitant Use with Insulin and Insulin Secretagogues:Increased risk of hypoglycemia when used in combination with insulin and/or an insulin secretagogue. Lower dose of insulin or insulin secretagogue may be required (5.3)

6 ADVERSE REACTIONS

For metformin hydrochloride tablets, the most common adverse reactions (>5.0%) are diarrhea, nausea/vomiting, flatulence, asthenia, indigestion, abdominal discomfort, and headache. (6.1)

To report SUSPECTED ADVERSE REACTIONS, contact Granules Pharmaceuticals Inc at 1-877-770-3183 or FDA at 1-800-FDA-1088 or www.fda.gov/medwatch

7 DRUG INTERACTIONS

- Carbonic anhydrase inhibitors may increase risk of lactic acidosis. Consider more frequent monitoring (7)
- Drugs that reduce metformin clearance (such as ranolazine, vandetanib, dolutegravir, and cimetidine) may increase the accumulation of metformin. Consider the benefits and risks of concomitant use (7)
- Alcohol can potentiate the effect of metformin on lactate metabolism. Warn patients against excessive alcohol intake (7)

8 USE IN SPECIFIC POPULATIONS

- Females and Males of Reproductive Potential: Advise premenopausal females of the potential for an unintended pregnancy. (8.3)
- Geriatric Use: Assess renal function more frequently. (8.5)
- Hepatic Impairment: Avoid use in patients with hepatic impairment. (8.7)

FULL PRESCRIBING INFORMATION

BOXED WARNING

WARNING: LACTIC ACIDOSIS
Postmarketing cases of metformin-associated lactic acidosis have resulted in death, hypothermia, hypotension, and resistant bradyarrhythmias. The onset of metformin associated lactic acidosis is often subtle, accompanied only by nonspecific symptoms such as malaise, myalgias, respiratory distress, somnolence, and abdominal pain. Metformin associated lactic acidosis was characterized by elevated blood lactate levels (>5 mmol/Liter), anion gap acidosis (without evidence of ketonuria or ketonemia), an increased lactate/pyruvate ratio; and metformin plasma levels generally >5 mcg/mL [see Warnings and Precautions (5.1)].
Risk factors for metformin-associated lactic acidosis include renal impairment, concomitant use of certain drugs (e.g. carbonic anhydrase inhibitors such as topiramate), age 65 years old or greater, having a radiological study with contrast, surgery and other procedures, hypoxic states (e.g., acute congestive heart failure), excessive alcohol intake, and hepatic impairment. Steps to reduce the risk of and manage metformin-associated lactic acidosis in these high risk groups are provided [see Dosage and Administration (2.3),(2.7), Contraindications (4), Warnings and Precautions (5.1)].
If metformin-associated lactic acidosis is suspected, immediately discontinue metformin hydrochloride tablets and institute general supportive measures in a hospital setting. Prompt hemodialysis is recommended [ see Warnings and Precautions (5.1)].

1 INDICATIONS & USAGE

Metformin hydrochloride tablets are indicated as an adjunct to diet and exercise to improve glycemic control in adults and pediatric patients 10 years of age and older with type 2 diabetes mellitus.

2 DOSAGE & ADMINISTRATION

2.1 Adult Dosage

Metformin Hydrochloride Tablets

- The recommended starting dose of metformin hydrochloride tablets are 500 mg orally twice a day or 850 mg once a day, given with meals.
- Increase the dose in increments of 500 mg weekly or 850 mg every 2 weeks on the basis of glycemic control and tolerability, up to a maximum dose of 2550 mg per day, given in divided doses.
- Doses above 2000 mg may be better tolerated given 3 times a day with meals.

2.2 Pediatric Dosage for metformin hydrochloride tablets

- The recommended starting dose of metformin hydrochloride tablets for pediatric patients 10 years of age and older is 500 mg orally twice a day, given with meals.
- Increase dosage in increments of 500 mg weekly on the basis of glycemic control and tolerability, up to a maximum of 2000 mg per day, given in divided doses twice daily.

2.3 Recommendations for Use in Renal Impairment

- Assess renal function prior to initiation of metformin hydrochloride tablets and periodically thereafter.
- Metformin hydrochloride tablets are contraindicated in patients with an estimated glomerular filtration rate (eGFR) below 30 mL/minute/1.73 m^2.
- Initiation of metformin hydrochloride tablets in patients with an eGFR between 30 to 45 mL/minute/1.73 m^2is not recommended.
- In patients taking metformin hydrochloride tablets whose eGFR later falls below 45 mL/min/1.73 m^2, assess the benefit risk of continuing therapy.
- Discontinue metformin hydrochloride tablets if the patient’s eGFR later falls below 30 mL/minute/1.73 m^2[ see Warnings and Precautions (5.1)] .

2.4 Discontinuation for Iodinated Contrast Imaging Procedures

Discontinue metformin hydrochloride tablets at the time of, or prior to, an iodinated contrast imaging procedure in patients with an eGFR between 30 and 60 mL/min/1.73 m^2; in patients with a history of liver disease, alcoholism, or heart failure; or in patients who will be administered intra-arterial iodinated contrast. Re-evaluate eGFR 48 hours after the imaging procedure; restart metformin hydrochloride tablets if renal function is stable.

3 DOSAGE FORMS & STRENGTHS

Metformin Hydrochloride Tablets, USP are available as:
• Tablets: 850 mg - White to off-white, round, biconvex, film coated tablets debossed with
G 11 on one side and plain on the other side.

4 CONTRAINDICATIONS

Metformin hydrochloride tablets are contraindicated in patients with:

- Severe renal impairment (eGFR below 30 mL/min/1.73 m^2) [ see Warnings and Precautions (5.1)].
- Hypersensitivity to metformin.
- Acute or chronic metabolic acidosis, including diabetic ketoacidosis, with or without coma.

5 WARNINGS AND PRECAUTIONS

5.1 Lactic Acidosis

There have been postmarketing cases of metformin-associated lactic acidosis, including fatal cases. These cases had a subtle onset and were accompanied by nonspecific symptoms such as malaise, myalgias, abdominal pain, respiratory distress, or increased somnolence; however, hypotension and resistant bradyarrhythmias have occurred with severe acidosis. Metformin associated lactic acidosis was characterized by elevated blood lactate concentrations (>5 mmol/L), anion gap acidosis (without evidence of ketonuria or ketonemia), and an increased lactate: pyruvate ratio; metformin plasma levels were generally >5 mcg/mL. Metformin decreases liver uptake of lactate increasing lactate blood levels which may increase the risk of lactic acidosis, especially in patients at risk.
If metformin-associated lactic acidosis is suspected, general supportive measures should be instituted promptly in a hospital setting, along with immediate discontinuation of metformin hydrochloride tablets. In metformin hydrochloride tablets treated patients with a diagnosis or strong suspicion of lactic acidosis, prompt hemodialysis is recommended to correct the acidosis and remove accumulated metformin (metformin hydrochloride is dialyzable with a clearance of up to 170 mL/min under good hemodynamic conditions). Hemodialysis has often resulted in reversal of symptoms and recovery.
Educate patients and their families about the symptoms of lactic acidosis and, if these symptoms occur, instruct them to discontinue metformin hydrochloride tablet and report these symptoms to their healthcare provider.
For each of the known and possible risk factors for metformin-associated lactic acidosis, recommendations to reduce the risk of and manage metformin-associated lactic acidosis are provided below:

- Renal impairment— The postmarketing metformin-associated lactic acidosis cases primarily occurred in patients with significant renal impairment.

The risk of metformin accumulation and metformin-associated lactic acidosis increases with the severity of renal impairment because metformin is substantially excreted by the kidney. Clinical recommendations based upon the patient’s renal function include [ see Dosage and Administration (2.1), Clinical Pharmacology (12.3)] :

-
  - Before initiating metformin hydrochloride tablets, obtain an estimated glomerular filtration rate (eGFR).
  - Metformin hydrochloride tablets are contraindicated in patients with an eGFR less than 30 mL/min/1.73 m^2[see Contraindications (4)].
  - Initiation of metformin hydrochloride tablets is not recommended in patients with eGFR between 30 to 45 mL/min/1.73 m^2.
  - Obtain an eGFR at least annually in all patients taking metformin hydrochloride tablets.
  - In patients at risk for the development of renal impairment (e.g., the elderly), renal function should be assessed more frequently.In patients taking metformin hydrochloride tablets whose eGFR falls below 45 mL/min/1.73 m^2, assess the benefit and risk of continuing therapy.
- Drug interactions—The concomitant use of metformin hydrochloride tablets with specific drugs may increase the risk of metformin-associated lactic acidosis: those that impair renal function, result in significant hemodynamic change, interfere with acid-base balance, or increase metformin accumulation. Consider more frequent monitoring of patients.
- Age 65 or greater—The risk of metformin-associated lactic acidosis increases with the patient’s age because elderly patients have a greater likelihood of having hepatic, renal, or cardiac impairment than younger patients. Assess renal function more frequently in elderly patients.
- Radiologic studies with contrast—Administration of intravascular iodinated contrast agents in metformin-treated patients has led to an acute decrease in renal function and the occurrence of lactic acidosis. Stop metformin hydrochloride tablets at the time of, or prior to, an iodinated contrast imaging procedure in patients with an eGFR between 30 and 60 mL/min/1.73 m^2; in patients with a history of hepatic impairment, alcoholism or heart failure; or in patients who will be administered intra-arterial iodinated contrast. Re-evaluate eGFR 48 hours after the imaging procedure, and restart metformin hydrochloride tablets if renal function is stable.
- Surgery and other procedures—Withholding of food and fluids during surgical or other procedures may increase the risk for volume depletion, hypotension, and renal impairment. Metformin hydrochloride tablets should be temporarily discontinued while patients have restricted food and fluid intake.
- Hypoxic states—Several of the postmarketing cases of metformin-associated lactic acidosis occurred in the setting of acute congestive heart failure (particularly when accompanied by hypoperfusion and hypoxemia). Cardiovascular collapse (shock), acute myocardial infarction, sepsis, and other conditions associated with hypoxemia have been associated with lactic acidosis and may cause prerenal azotemia. When such an event occurs, discontinue metformin hydrochloride tablets.
- Excessive alcohol intake—Alcohol potentiates the effect of metformin on lactate metabolism. Patients should be warned against excessive alcohol intake while receiving metformin hydrochloride tablets.
- Hepatic impairment—Patients with hepatic impairment have developed cases of metformin- associated lactic acidosis. This may be due to impaired lactate clearance resulting in higher lactate blood levels. Therefore, avoid use of metformin hydrochloride tablets in patients with clinical or laboratory evidence of hepatic disease.

5.2 Vitamin B12 Deficiency

In metformin hydrochloride tablets clinical trials of 29-week duration, a decrease to subnormal levels of previously normal serum vitamin B12levels was observed in approximately 7% of patients. Such decrease, possibly due to interference with B12absorption from the B12-intrinsic factor complex, may be associated with anemia but appears to be rapidly reversible with discontinuation of metformin hydrochloride tablets or vitamin B12supplementation. Certain individuals (those with inadequate vitamin B12or calcium intake or absorption) appear to be predisposed to developing subnormal vitamin B12levels. Measure hematologic parameters on an annual basis and vitamin B12at 2 to 3 year intervals in patients on metformin hydrochloride tablets and manage any abnormalities [see Adverse Reactions (6.1)].

5.3 Hypoglycemia with Concomitant Use with Insulin and Insulin Secretagogues

Insulin and insulin secretagogues (e.g., sulfonylurea) are known to cause hypoglycemia. Metformin hydrochloride tablets may increase the risk of hypoglycemia when combined with insulin and/or an insulin secretagogue. Therefore, a lower dose of insulin or insulin secretagogue may be required to minimize the risk of hypoglycemia when used in combination with metformin hydrochloride tablet [ see Drug Interactions (7)].

5.4 Macrovascular Outcomes

There have been no clinical studies establishing conclusive evidence of macrovascular risk reduction with metformin hydrochloride tablets.

6 ADVERSE REACTIONS

The following adverse reactions are also discussed elsewhere in the labeling:

- Lactic Acidosis [ see Boxed Warningand Warnings and Precautions (5.1)].
- Vitamin B12Deficiency [ see Warnings and Precautions (5.2)].
- Hypoglycemia [ see Warnings and Precautions (5.3)

6.1 Clinical Studies Experience

Because clinical trials are conducted under widely varying conditions, adverse reaction rates observed in the clinical trials of a drug cannot be directly compared to rates in the clinical trials of another drug and may not reflect the rates observed in practice.

Metformin Hydrochloride Tablets

In a U.S. clinical trial of metformin hydrochloride tablets in patients with type 2 diabetes mellitus, a total of 141 patients received metformin hydrochloride tablets up to 2550 mg per day. Adverse reactions reported in greater than 5% of metformin hydrochloride tablets treated patients and that were more common than in placebo-treated patients, are listed in Table 1.

Table 1: Adverse Reactions from a Clinical Trial of Metformin Hydrochloride Tablets Occurring >5% and More Common than Placebo in Patients with Type 2 Diabetes Mellitus

 | Metformin Hydrochloride Tablets (n=141) | Placebo (n=145)
Diarrhea | 53% | 12%
Nausea/Vomiting | 26% | 8%
Flatulence | 12% | 6%
Asthenia | 9% | 6%
Indigestion | 7% | 4%
Abdominal Discomfort | 6% | 5%
Headache | 6% | 5%

Diarrhea led to discontinuation of metformin hydrochloride tablets in 6% of patients. Additionally, the following adverse reactions were reported in ≥1 % to ≤5% of metformin hydrochloride tablets treated patients and were more commonly reported with metformin hydrochloride tablets than placebo: abnormal stools, hypoglycemia, myalgia, lightheaded, dyspnea, nail disorder, rash, sweating increased, taste disorder, chest discomfort, chills, flu syndrome, flushing, palpitation.

In metformin hydrochloride tablets clinical trials of 29-week duration, a decrease to subnormal levels of previously normal serum vitamin B12levels was observed in approximately 7% of patients.

Pediatric Patients

In clinical trials with metformin hydrochloride tablets in pediatric patients with type 2 diabetes mellitus, the profile of adverse reactions was similar to that observed in adults.

6.2 Postmarketing Experience

The following adverse reactions have been identified during post approval use of metformin. Because these reactions are reported voluntarily from a population of uncertain size, it is not always possible to reliably estimate their frequency or establish a causal relationship to drug exposure.
Cholestatic, hepatocellular, and mixed hepatocellular liver injury have been reported with postmarketing use of metformin.

7 DRUG INTERACTIONS

Table 3 presents clinically significant drug interactions with metformin hydrochloride tablets.
Table 3: Clinically Significant Drug Interactions with Metformin Hydrochloride Tablets

Carbonic Anhydrase Inhibitors
Clinical Impact: | Carbonic anhydrase inhibitors frequently cause a decrease in serum bicarbonate and induce non-anion gap, hyperchloremic metabolic acidosis. Concomitant use of these drugs with metformin hydrochloride tablets may increase the risk for lactic acidosis.
Intervention: | Consider more frequent monitoring of these patients.
Examples: | Topiramate, zonisamide, acetazolamide or dichlorphenamide.
Drugs that Reducemetformin hydrochloride tablet Clearance
Clinical Impact: | Concomitant use of drugs that interfere with common renal tubular transport systems involved in the renal elimination of metformin (e.g., organic cationic transporter-2 [OCT2] / multidrug and toxin extrusion [MATE] inhibitors) could increase systemic exposure to metformin and may increase the risk for lactic acidosis [ see Clinical Pharmacology (12.3)].
Intervention: | Consider the benefits and risks of concomitant use with metformin hydrochloride tablets.
Examples: | Ranolazine, vandetanib, dolutegravir, and cimetidine.
Alcohol
Clinical Impact: | Alcohol is known to potentiate the effect of metformin on lactate metabolism.
Intervention: | Warn patients against excessive alcohol intake while receiving metformin hydrochloride tablets.
Insulin Secretagogues or Insulin
Clinical Impact: | Coadministration of metformin hydrochloride tablets with an insulin secretagogue (e.g., sulfonylurea) or insulin may increase the risk of hypoglycemia.
Intervention: | Patients receiving an insulin secretagogue or insulin may require lower doses of the insulin secretagogue or insulin.
Drugs Affecting Glycemic Control
Clinical Impact: | Certain drugs tend to produce hyperglycemia and may lead to loss of glycemic control.
Intervention: | When such drugs are administered to a patient receiving metformin hydrochloride tablets, observe the patient closely for loss of blood glucose control. When such drugs are withdrawn from a patient receiving metformin hydrochloride tablets, observe the patient closely for hypoglycemia.
Examples: | Thiazides and other diuretics, corticosteroids, phenothiazines, thyroid products, estrogens, oral contraceptives, phenytoin, nicotinic acid, sympathomimetics, calcium channel blockers, and isoniazid.

8 USE IN SPECIFIC POPULATIONS

8.1 Pregnancy

Risk Summary
Limited data with metformin hydrochloride tablets in pregnant women are not sufficient to determine a drug-associated risk for major birth defects or miscarriage. Published studies with metformin use during pregnancy have not reported a clear association with metformin and major birth defect or miscarriage risk [see Data] .There are risks to the mother and fetus associated with poorly controlled diabetes mellitus in pregnancy [see Clinical Considerations] .
No adverse developmental effects were observed when metformin was administered to pregnant Sprague Dawley rats and rabbits during the period of organogenesis at doses up to 2- and 5-times, respectively, a 2550 mg clinical dose, based on body surface area [see Data] .

The estimated background risk of major birth defects is 6 to 10% in women with pre-gestational diabetes mellitus with an HbA1C >7 and has been reported to be as high as 20 to 25% in women with a HbA1C > 10. The estimated background risk of miscarriage for the indicated population is unknown. In the U.S. general population, the estimated background risk of major birth defects and miscarriage in clinically recognized pregnancies is 2 to 4% and 15 to 20%, respectively.
Clinical Considerations
Disease-associated maternal and/or embryo/fetal risk
Poorly-controlled diabetes mellitus in pregnancy increases the maternal risk for diabetic ketoacidosis, pre-eclampsia, spontaneous abortions, preterm delivery, stillbirth and delivery complications. Poorly controlled diabetes mellitus increases the fetal risk for major birth defects, stillbirth, and macrosomia related morbidity.

Data
Human Data
Published data from post-marketing studies have not reported a clear association with metformin and major birth defects, miscarriage, or adverse maternal or fetal outcomes when metformin was used during pregnancy. However, these studies cannot definitely establish the absence of any metformin-associated risk because of methodological limitations, including small sample size and inconsistent comparator groups.

Animal Data
Metformin hydrochloride did not adversely affect development outcomes when administered to pregnant rats and rabbits at doses up to 600 mg/kg/day. This represents an exposure of about 2 and 5 times a 2550 mg clinical dose based on body surface area comparisons for rats and rabbits, respectively. Determination of fetal concentrations demonstrated a partial placental barrier to metformin.

8.2 Lactation

Risk Summary

Limited published studies report that metformin is present in human milk [see Data] .However, there is insufficient information to determine the effects of metformin on the breastfed infant and no available information on the effects of metformin on milk production. Therefore, the developmental and health benefits of breastfeeding should be considered along with the mother’s clinical need for metformin hydrochloride tablets and any potential adverse effects on the breastfed child from metformin hydrochloride tablets or from the underlying maternal condition.

Data

Published clinical lactation studies report that metformin is present in human milk which resulted in infant doses approximately 0.11 % to 1% of the maternal weight-adjusted dosage and a milk/plasma ratio ranging between 0.13 and 1. However, the studies were not designed to definitely establish the risk of use of metformin during lactation because of small sample size and limited adverse event data collected in infants.

8.3 Females and Males of Reproductive Potential

Discuss the potential for unintended pregnancy with premenopausal women as therapy with metformin hydrochloride tablets may result in ovulation in some anovulatory women.

8.4 Pediatric Use

Metformin Hydrochloride Tablets

The safety and effectiveness of metformin hydrochloride tablets for the treatment of type 2 diabetes mellitus have been established in pediatric patients 10 to 16 years old. Safety and effectiveness of metformin hydrochloride tablets have not been established in pediatric patients less than 10 years old.

Use of metformin hydrochloride tablets in pediatric patients 10 to 16 years old for the treatment of type 2 diabetes mellitus is supported by evidence from adequate and well-controlled studies of metformin hydrochloride tablets in adults with additional data from a controlled clinical study in pediatric patients 10 to 16 years old with type 2 diabetes mellitus, which demonstrated a similar response in glycemic control to that seen in adults [ see Clinical Studies (14.1)] .In this study, adverse reactions were similar to those described in adults. A maximum daily dose of 2000 mg of metformin hydrochloride tablets is recommended. [ see Dosage and Administration (2.2). ].

8.5 Geriatric Use

Controlled clinical studies of metformin hydrochloride tablets did not include sufficient numbers of elderly patients to determine whether they respond differently from younger patients. In general, dose selection for an elderly patient should be cautious, usually starting at the low end of the dosing range, reflecting the greater frequency of decreased hepatic, renal, or cardiac function, and of concomitant disease or other drug therapy and the higher risk of lactic acidosis. Assess renal function more frequently in elderly patients [see Warnings and Precautions (5.1).

8.6 Renal Impairment

Metformin is substantially excreted by the kidney, and the risk of metformin accumulation and lactic acidosis increases with the degree of renal impairment. Metformin hydrochloride tablets are contraindicated in severe renal impairment, patients with an estimated glomerular filtration rate (eGFR) below 30 mL/min/1.73 m^2[ see Dosage and Administration (2.3), Contraindications (4), Warnings and Precautions (5.1), and Clinical Pharmacology (12.3)] .

8.7 Hepatic Impairment

Use of metformin in patients with hepatic impairment has been associated with some cases of lactic acidosis. Metformin hydrochloride tablets are not recommended in patients with hepatic impairment. [ see Warnings and Precautions (5.1)].

10 OVERDOSAGE

Overdose of metformin hydrochloride has occurred, including ingestion of amounts greater than 50 grams. Hypoglycemia was reported in approximately 10% of cases, but no causal association with metformin has been established. Lactic acidosis has been reported in approximately 32% of metformin overdose cases [see Warnings and Precautions (5.1)] .
Metformin is dialyzable with a clearance of up to 170 mL/min under good hemodynamic conditions. Therefore, hemodialysis may be useful for removal of accumulated drug from patients in whom metformin overdosage is suspected.

11 DESCRIPTION

Metformin hydrochloride tablets, USP contain the antihyperglycemic agent metformin, which is a biguanide, in the form of monohydrochloride. The chemical name of metformin hydrochloride is N,N-dimethylimidodicarbonimidic diamide hydrochloride.

Metformin hydrochloride, USP is a white to off-white crystalline compound with a molecular formula of C4H11N5• HCl and a molecular weight of 165.63. Metformin hydrochloride is freely soluble in water, slightly soluble in alcohol, practically insoluble in acetone and in methylene chloride. The pKa of metformin is 12.4. The pH of a 1% aqueous solution of metformin hydrochloride is 6.68.

Metformin hydrochloride tablets, USP contain 500 mg, 850 mg, or 1000 mg of metformin hydrochloride. Each tablet contains the inactive ingredients povidone (K-30), Povidone (K-90), pregelatinized starch, and magnesium stearate. In addition, the coating for the tablet contains artificial blackberry flavor, hypromellose, macrogol and titanium dioxide.

12 CLINICAL PHARMACOLOGY

12.1 Mechanism of Action

Metformin is an antihyperglycemic agent which improves glucose tolerance in patients with type 2 diabetes mellitus, lowering both basal and postprandial plasma glucose. Metformin decreases hepatic glucose production, decreases intestinal absorption of glucose, and improves insulin sensitivity by increasing peripheral glucose uptake and utilization. With metformin therapy, insulin secretion remains unchanged while fasting insulin levels and day-long plasma insulin response may decrease.

12.3 Pharmacokinetics

Absorption
The absolute bioavailability of a metformin hydrochloride tablets 500 mg given under fasting conditions is approximately 50% to 60%. Studies using single oral doses of metformin hydrochloride tablets 500 to 1500 mg and 850 to 2550 mg, indicate that there is a lack of dose proportionality with increasing doses, which is due to decreased absorption rather than an alteration in elimination. At usual clinical doses and dosing schedules of metformin hydrochloride tablets, steady state plasma concentrations of metformin are reached within 24 to 48 hours and are generally <1 μg/mL.
Following a single oral dose of metformin hydrochloride extended-release tablets, Cmaxis achieved with a median value of 7 hours and a range of 4 to 8 hours. Peak plasma levels are approximately 20% lower compared to the same dose of metformin hydrochloride tablets, however, the extent of absorption (as measured by AUC) is comparable to metformin hydrochloride tablets.
At steady state, the AUC and Cmaxare less than dose proportional for metformin hydrochloride extended-release tablets within the range of 500 to 2000 mg administered once daily. Peak plasma levels are approximately 0.6, 1.1, 1.4 and 1.8 mcg/mL for 500, 1000, 1500, and 2000 mg once-daily doses, respectively. The extent of metformin absorption (as measured by AUC) from metformin hydrochloride extended-release tablets at a 2000 mg once-daily dose is similar to the same total daily dose administered as metformin hydrochloride tablets 1000 mg twice daily. After repeated administration of metformin hydrochloride extended-release tablets, metformin did not accumulate in plasma.
Effect of food: Food decreases the extent of absorption and slightly delays the absorption of metformin, as shown by approximately a 40% lower mean peak plasma concentration (Cmax), a 25% lower area under the plasma concentration versus time curve (AUC), and a 35-minute prolongation of time to peak plasma concentration (Tmax) following administration of a single 850 mg tablet of metformin hydrochloride tablets with food, compared to the same tablet strength administered fasting.
Distribution
The apparent volume of distribution (V/F) of metformin following single oral doses of metformin hydrochloride tablets 850 mg averaged 654 ± 358 L. Metformin is negligibly bound to plasma proteins. Metformin partitions into erythrocytes, most likely as a function of time.
Metabolism
Intravenous single-dose studies in normal subjects demonstrate that metformin is excreted unchanged in the urine and does not undergo hepatic metabolism (no metabolites have been identified in humans) nor biliary excretion.
Elimination
Renal clearance (see Table 4) is approximately 3.5 times greater than creatinine clearance, which indicates that tubular secretion is the major route of metformin elimination. Following oral administration, approximately 90% of the absorbed drug is eliminated via the renal route within the first 24 hours, with a plasma elimination half-life of approximately 6.2 hours. In blood, the elimination half-life is approximately 17.6 hours, suggesting that the erythrocyte mass may be a compartment of distribution.
Specific Populations
Renal Impairment
In patients with decreased renal function the plasma and blood half-life of metformin is prolonged and the renal clearance is decreased (see Table 3) [see Dosage and Administration (2.3), Contraindications (4), Warnings and Precautions (5.1)and Use in Specific Populations (8.6)].
Hepatic Impairment
No pharmacokinetic studies of metformin have been conducted in patients with hepatic impairment [See Warnings and Precautions (5.1)and Use in Specific Populations (8.7)]. Geriatrics

Limited data from controlled pharmacokinetic studies of metformin hydrochloride tablets in healthy elderly subjects suggest that total plasma clearance of metformin is decreased, the half-life is prolonged, and Cmaxis increased, compared to healthy young subjects. It appears that the change in metformin pharmacokinetics with aging is primarily accounted for by a change in renal function (see Table 4). [see Warnings and Precautions (5.1)and Use in Specific Populations (8.5) ].

Table 4: Select Mean (±S.D.) Metformin Pharmacokinetic Parameters Following Single or Multiple Oral Doses of Metformin Hydrochloride Tablets

Subject Groups: Metformin Hydrochloride Tablet dosea (number of subjects) | Cmaxb (mcg/mL) | Tmaxc (hrs) | Renal Clearance (mL/min)
Healthy, nondiabetic adults: 500 mg single dose (24) 850 mg single dose (74)d 850 mg three times daily for 19 dosese(9) | 1.03 (±0.33) 1.60 (±0.38) 2.01 (±0.42) | 2.75 (±0.81) 2.64 (±0.82) 1.79 (±0.94) | 600 (±132) 552 (±139) 642 (±173)
Adults with type 2 diabetes mellitus: 850 mg single dose (23) 850 mg three times daily for 19 dosese (9) | 1.48 (±0.5) 1.90 (±0.62) | 3.32 (±1.08) 2.01 (±1.22) | 491 (±138) 550 (±160)
Elderlyf, healthy nondiabetic adults: 850 mg single dose (12) | 2.45 (±0.70) | 2.71 (±1.05) | 412 (±98)
Renal-impaired adults: 850 mg single dose Mild(CLcr g61 to 90 mL/min) (5) Moderate(CLcr 31 to 60 mL/min) (4) Severe(CLcr 10 to 30 mL/min) (6) | 1.86 (±0.52) 4.12 (±1.83) 3.93 (±0.92) | 3.20 (±0.45) 3.75 (±0.50) 4.01 (±1.10) | 384 (±122) 108 (±57) 130 (±90)

aAll doses given fasting except the first 18 doses of the multiple dose studies

bPeak plasma concentration

cTime to peak plasma concentration

dCombined results (average means) of five studies: mean age 32 years (range 23 to 59 years)

eKinetic study done following dose 19, given fasting

fElderly subjects, mean age 71 years (range 65 to 81 years)

gCLcr= creatinine clearance normalized to body surface area of 1.73 m^2

Pediatrics
After administration of a single oral metformin hydrochloride 500 mg tablet with food, geometric mean metformin Cmaxand AUC differed less than 5% between pediatric type 2 diabetic patients (12 to 16 years of age) and gender- and weight-matched healthy adults (20 to 45 years of age), all with normal renal function.

Gender
Metformin pharmacokinetic parameters did not differ significantly between normal subjects and patients with type 2 diabetes mellitus when analyzed according to gender (males=19, females=16).

Race
No studies of metformin pharmacokinetic parameters according to race have been performed.

Drug Interactions

In Vivo Assessment of Drug Interactions

Table 5: Effect of Coadministered Drug on Plasma Metformin Systemic Exposure

Coadministered Drug | Dose of Coadministered Drug* | Dose of Metformin* | Geometric Mean Ratio (ratio with/without coadministered drug) No Effect=1.00
Coadministered Drug | Dose of Coadministered Drug* | Dose of Metformin* |  | AUC† | Cmax
No dosing adjustments required for the following:
Glyburide | 5 mg | 850 mg | metformin | 0.91‡ | 0.93‡
Furosemide | 40 mg | 850 mg | metformin | 1.09‡ | 1.22‡
Nifedipine | 10 mg | 850 mg | metformin | 1.16 | 1.21
Propranolol | 40 mg | 850 mg | metformin | 0.90 | 0.94
Ibuprofen | 400 mg | 850 mg | metformin | 1.05‡ | 1.07‡
Cationic drugs eliminated by renal tubular secretion may reduce metformin elimination[see Warnings and Precautions (5.9)and Drug Interactions (7.2). ]
Cimetidine | 400 mg | 850 mg | metformin | 1.40 | 1.61
Carbonic anhydrase inhibitors may cause metabolic acidosis[see Warnings and Precautions (5.1)and Drug Interactions (7.1).]
Topiramate | 100 mg§ | 500 mg§ | metformin | 1.25§ | 1.17

*All metformin and coadministered drugs were given as single doses

†AUC = AUC (INF)

‡Ratio of arithmetic means

§At steady state with topiramate 100 mg every 12 hours and metformin 500 mg every 12 hours;

AUC = AUC0-12h

Table 6: Effect of Metformin on Coadministered Drug Systemic Exposure

Coadministered Drug | Dose of Coadministered Drug* | Dose of Metformin* | Geometric Mean Ratio (ratio with/without metformin) No Effect=1.00
Coadministered Drug | Dose of Coadministered Drug* | Dose of Metformin* |  | AUC† | Cmax
No dosing adjustments required for the following:
Glyburide | 5 mg | 850 mg | glyburide | 0.78‡ | 0.63‡
Furosemide | 40 mg | 850 mg | furosemide | 0.87‡ | 0.69‡
Nifedipine | 10 mg | 850 mg | nifedipine | 1.10§ | 1.08
Propranolol | 40 mg | 850 mg | propranolol | 1.01§ | 1.02
Ibuprofen | 400 mg | 850 mg | ibuprofen | 0.97¶ | 1.01¶
Cimetidine | 400 mg | 850 mg | cimetidine | 0.95§ | 1.01

*All metformin and coadministered drugs were given as single doses

†AUC = AUC(INF) unless otherwise noted

‡Ratio of arithmetic means, p-value of difference <0.05

§AUC(0-24 hr) reported

¶Ratio of arithmetic means

13 NONCLINICAL TOXICOLOGY

13.1 Carcinogenesis & Mutagenesis & Impairment Of Fertility

Long-term carcinogenicity studies have been performed in rats (dosing duration of 104 weeks) and mice (dosing duration of 91 weeks) at doses up to and including 900 mg/kg/day and 1500 mg/kg/day, respectively. These doses are both approximately 3 times the maximum recommended human daily dose of 2550 mg based on body surface area comparisons. No evidence of carcinogenicity with metformin was found in either male or female mice. Similarly, there was no tumorigenic potential observed with metformin in male rats. There was, however, an increased incidence of benign stromal uterine polyps in female rats treated with 900 mg/kg/day.

There was no evidence of a mutagenic potential of metformin in the following in vitrotests: Ames test (S. typhimurium),gene mutation test (mouse lymphoma cells), or chromosomal aberrations test (human lymphocytes). Results in the in vivomouse micronucleus test were also negative.

Fertility of male or female rats was unaffected by metformin when administered at doses as high as 600 mg/kg/day, which is approximately 2 times the maximum recommended human daily dose of 2550 mg based on body surface area comparisons.

14 CLINICAL STUDIES

14.1 Metformin Hydrochloride Tablets

Adult Clinical Studies

A double-blind, placebo-controlled, multicenter US clinical trial involving obese patients with type 2 diabetes mellitus whose hyperglycemia was not adequately controlled with dietary management alone (baseline fasting plasma glucose [FPG] of approximately 240 mg/dL) was conducted. Patients were treated with metformin hydrochloride tablets (up to 2550 mg/day) or placebo for 29 weeks. The results are presented in Table 7.

Table 7: Mean Change in Fasting Plasma Glucose and HbA1c at Week 29 Comparing Metformin Hydrochloride Tablets vs Placebo in Patients with Type 2 Diabetes Mellitus

 | Metformin Hydrochloride Tablets (n=141) | Placebo (n=145) | p-Value
FPG (mg/dL)
Baseline | 241.5 | 237.7 | NS*
Change at FINAL VISIT | –53.0 | 6.3 | 0.001
Hemoglobin A 1c (%)
Baseline | 8.4 | 8.2 | NS*
Change at FINAL VISIT | –1.4 | 0.4 | 0.001

*Not statistically significant

Mean baseline body weight was 201 lbs and 206 lbs in the metformin hydrochloride tablets and placebo arms, respectively. Mean change in body weight from baseline to week 29 was -1.4 lbs and -2.4 lbs in the metformin hydrochloride tablets and placebo arms, respectively. A 29-week, double -blind, placebo-controlled study of metformin hydrochloride tablets and glyburide, alone and in combination, was conducted in obese patients with type 2 diabetes mellitus who had failed to achieve adequate glycemic control while on maximum doses of glyburide (baseline FPG of approximately 250 mg/dL). Patients randomized to the combination arm started therapy with metformin hydrochloride tablets 500 mg and glyburide 20 mg. At the end of each week of the first 4 weeks of the trial, these patients had their dosages of metformin hydrochloride tablets increased by 500 mg if they had failed to reach target fasting plasma glucose. After week 4, such dosage adjustments were made monthly, although no patient was allowed to exceed metformin hydrochloride tablets 2500 mg. Patients in the metformin hydrochloride tablets only arm (metformin plus placebo) discontinued glyburide and followed the same titration schedule. Patients in the glyburide arm continued the same dose of glyburide. At the end of the trial, approximately 70% of the patients in the combination group were taking metformin hydrochloride tablets 2000 mg/glyburide 20 mg or metformin hydrochloride tablets 2500 mg/glyburide 20 mg. The results are displayed in Table 8.

Table 8: Mean Change in Fasting Plasma Glucose and HbA1c at Week 29 Comparing Metformin Hydrochloride Tablets /Glyburide (Comb) vs Glyburide (Glyb) vs Metformin Hydrochloride Tablets (MET): in Patients with Type 2 Diabetes Mellitus with Inadequate Glycemic Control on Glyburide

 |  |  | MET (n=210) | p-Values
 | Comb (n=213) | Glyb (n=209) | MET (n=210) | Glyb vs Comb | MET vs Comb | MET vs Glyb
Fasting Plasma Glucose (mg/dL)
Baseline | 250.5 | 247.5 | 253.9 | NS* | NS* | NS*
Change at FINAL VISIT | –63.5 | 13.7 | –0.9 | 0.001 | 0.001 | 0.025
Hemoglobin A 1c (%)
Baseline | 8.8 | 8.5 | 8.9 | NS* | NS* | 0.007
Change at FINAL VISIT | –1.7 | 0.2 | –0.4 | 0.001 | 0.001 | 0.001

*Not statistically significant

Mean baseline body weight was 202 lbs, 203 lbs, and 204 lbs in the metformin hydrochloride tablets /glyburide, glyburide, and metformin hydrochloride tablets arms, respectively. Mean change in body weight from baseline to week 29 was 0.9 lbs, -0.7 lbs, and -8.4 lbs in the metformin hydrochloride tablets /glyburide, glyburide, and metformin hydrochloride tablets arms, respectively.

Pediatric Clinical Studies

A double-blind, placebo-controlled study in pediatric patients aged 10 to 16 years with type 2 diabetesmellitus (mean FPG 182.2 mg/dL), treatment with metformin hydrochloride tablets (up to 2000 mg/day) for up to 16 weeks (mean duration of treatment 11 weeks) was conducted. The results are displayed in Table 9.

Table 9: Mean Change in Fasting Plasma Glucose at Week 16 Comparing Metformin Hydrochloride Tablets vs Placebo in Pediatric Patientsawith Type 2 Diabetes Mellitus

 | Metformin Hydrochloride Tablets | Placebo | p-Value
FPG (mg/dL) | (n=37) | (n=36)
Baseline | 162.4 | 192.3
Change at FINAL VISIT | –42.9 | 21.4 | <0.001

aPediatric patients mean age 13.8 years (range 10 to 16 years)

Mean baseline body weight was 205 lbs and 189 lbs in the metformin hydrochloride tablets and placebo arms, respectively. Mean change in body weight from baseline to week 16 was -3.3 lbs and -2.0 lbs in the metformin hydrochloride tablets and placebo arms, respectively.

14.2 Metformin Hydrochloride Extended-Release Tablets

A 24-week, double-blind, randomized study of metformin hydrochloride extended-release tablets, taken twice daily (with breakfast and evening meal), was conducted in patients with type 2 diabetes mellitus who had been treated with metformin hydrochloride tablets 500 mg twice daily for at least 8 weeks prior to study entry. The results are shown in Table 11.

Table 11: Mean Changes from Baseline*in HbA1c and Fasting Plasma Glucose at Week 24 comparing Metformin Hydrochloride Tablets vs Metformin Hydrochloride Extended-Release Tabletsin Patients with Type 2 Diabetes Mellitus

 | Metformin Hydrochloride Tablets 500 mg Twice Daily | Metformin Hydrochloride Extended – release Tablets
 | Metformin Hydrochloride Tablets 500 mg Twice Daily | 1000 mgOnce Daily | 1500 mg Once Daily
Hemoglobin A1c(%) Baseline Change at FINAL VISIT (95% CI) | (n=67) | (n=72) | (n=66)
Hemoglobin A1c(%) Baseline Change at FINAL VISIT (95% CI) | 7.06 | 6.99 | 7.02
Hemoglobin A1c(%) Baseline Change at FINAL VISIT (95% CI) | 0.14a | 0.27 | 0.13
Hemoglobin A1c(%) Baseline Change at FINAL VISIT (95% CI) | (–0.04, 0.31) | (0.11, 0.43) | (–0.02, 0.28)
FPG(mg/dL) Baseline Change at FINAL VISIT (95% CI) | (n=69) | (n=72) | (n=70)
FPG(mg/dL) Baseline Change at FINAL VISIT (95% CI) | 127.2 | 131.0 | 131.4
FPG(mg/dL) Baseline Change at FINAL VISIT (95% CI) | 14.0 | 11.5 | 7.6
FPG(mg/dL) Baseline Change at FINAL VISIT (95% CI) | (7.0, 21.0) | (4.4, 18.6) | (1.0, 14.2)

†an=68
Mean baseline body weight was 210 lbs, 203 lbs and 193 lbs in the metformin hydrochloride tablets 500 mg twice daily, and metformin hydrochloride extended-release tablets 1000 mg and 1500 mg once daily arms, respectively. Mean change in body weight from baseline to week 24 was 0.9 lbs, 1.1 lbs and 0.9 lbs, respectively.

16 HOW SUPPLIED/STORAGE AND HANDLING

850 mg White to off-white, round, biconvex, film coated tablets debossing G on 11

one side and plain on the other side.

NDC: 70518-3084-00

NDC: 70518-3084-01

NDC: 70518-3084-02

NDC: 70518-3084-03

NDC: 70518-3084-04

NDC: 70518-3084-05

NDC: 70518-3084-06

NDC: 70518-3084-07

PACKAGING: 30 in 1 BLISTER PACK

PACKAGING: 180 in 1 BOTTLE PLASTIC

PACKAGING: 90 in 1 BOTTLE PLASTIC

PACKAGING: 30 in 1 BLISTER PACK

PACKAGING: 90 in 1 BOTTLE PLASTIC

PACKAGING: 30 in 1 BLISTER PACK

PACKAGING: 180 in 1 BOTTLE PLASTIC

PACKAGING: 100 in 1 BOTTLE PLASTIC

Store at 20º to 25º C (68º to 77º F); excursions permitted to 15º to 30º C (59º to 86º F). [see USP Controlled Room Temperature.]

Dispense in tight, light-resistant containers with child-resistant closure.

Repackaged and Distributed By:

Remedy Repack, Inc.

625 Kolter Dr. Suite #4 Indiana, PA 1-724-465-8762

17 PATIENT COUNSELING INFORMATION

Advise the patient to read the FDA-approved patient labeling (Patient Information).
Lactic Acidosis:
Explain the risks of lactic acidosis, its symptoms, and conditions that predispose to its development. Advise patients to discontinue metformin hydrochloride tablets immediately and to promptly notify their healthcare provider if unexplained hyperventilation, myalgias, malaise, unusual somnolence or other nonspecific symptoms occur. Counsel patients against excessive alcohol intake and inform patients about importance of regular testing of renal function while receiving metformin hydrochloride tablets. Instruct patients to inform their doctor that they are taking metformin hydrochloride tablets prior to any surgical or radiological procedure, as temporary discontinuation may be required [ see Warnings and Precautions (5.1)].
Hypoglycemia
Inform patients that hypoglycemia may occur when metformin hydrochloride tablets is coadministered with oral sulfonylureas and insulin. Explain to patients receiving concomitant therapy the risks of hypoglycemia, its symptoms and treatment, and conditions that predispose to its development [ see Warnings and Precautions (5.3)].

Vitamin B12 Deficiency:

Inform patients about importance of regular hematological parameters while receiving metformin hydrochloride tablets [ see Warnings and Precautions (5.2)].

Females of Reproductive Age:

Inform females that treatment with metformin hydrochloride tablets may result in ovulation in some premenopausal anovulatory women which may lead to unintended pregnancy [ see Use in Specific Populations (8.3)].

Repackaged By / Distributed By: RemedyRepack Inc.

625 Kolter Drive, Indiana, PA 15701

(724) 465-8762

.

PATIENT INFORMATION

.

PATIENT INFORMATION

Metformin Hydrochloride Tablets

(met-FOR-min HYE-droe-KLOR-ide)

Read the Patient Information that comes with metformin hydrochloride tablets before you start taking it and each time you get a refill. There may be new information. This leaflet does not take the place of talking with your healthcare provider about your medical condition or treatment.

What is the most important information I should know about metformin hydrochloride tablets?

Serious side effects can happen in people taking metformin hydrochloride tablets, including:
Lactic Acidosis.Metformin hydrochloride, the medicine in metformin hydrochloride tablets, can cause a rare, but serious, side effect called lactic acidosis (a build-up of lactic acid in the blood) that can cause death. Lactic acidosis is a medical emergency and must be treated in a hospital.
Stop taking metformin hydrochloride tablets and call your healthcare provider right away if you get any of the following symptoms of lactic acidosis:

- feel very weak and tired
- have unusual (not normal) muscle pain
- have trouble breathing
- have unusual sleepiness or sleep longer than usual
- have unexplained stomach or intestinal problems with nausea and vomiting, or diarrhea
- feel cold, especially in your arms and legs
- feel dizzy or lightheaded
- have a slow or irregular heartbeat

You have a higher chance of getting lactic acidosis if you:

- have kidney problems. People whose kidneys are not working properly should not take metformin hydrochloride tablets.
- have liver problems.
- have congestive heart failure that requires treatment with medicines.
- drink a lot of alcohol (very often or short-term “binge” drinking).
- get dehydrated (lose a large amount of body fluids). This can happen if you are sick with a fever,vomiting, or diarrhea. Dehydration can also happen when you sweat a lot with activity or exercise and do not drink enough fluids.
- have certain x-ray tests with injectable dyes or contrast agents.
- have surgery.
- have a heart attack, severe infection, or stroke.
- are 80 years of age or older and have not had your kidney function tested.

What are metformin hydrochloride tablets?

- Metformin hydrochloride tablets are prescription medicines that contain metformin hydrochloride. Metformin hydrochloride tablets are used with diet and exercise to help control high blood sugar (hyperglycemia) in adults with type 2 diabetes.
- Metformin hydrochloride tablets are not for people with type 1 diabetes.
- Metformin hydrochloride tablets are not for people with diabetic ketoacidosis (increased ketones in your blood or urine).

Metformin hydrochloride tablets help control your blood sugar in a number of ways. These include helping your body respond better to the insulin it makes naturally, decreasing the amount of sugar your liver makes, and decreasing the amount of sugar your intestines absorb. Metformin hydrochloride tablets do not cause your body to make more insulin.
Who should not take metformin hydrochloride tablets?

Some conditions increase your chance of getting lactic acidosis, or cause other problems if you take either of these medicines. Most of the conditions listed below can increase your chance of getting lactic acidosis.
Do not take metformin hydrochloride tablets if you:

- have kidney problems
- are allergic to the metformin hydrochloride in metformin hydrochloride tablets or any of the ingredients in metformin hydrochloride tablets. See the end of this leaflet for a complete list of ingredients in metformin hydrochloride tablets.
- are going to get an injection of dye or contrast agents for an x-ray procedure or if you are going to have surgery and not able to eat or drink much. In these situations, metformin hydrochloride tablets will need to be stopped for a short time. Talk to your healthcare provider about when you should stop metformin hydrochloride tablets and when you should start metformin hydrochloride Tablets again. see “ What is the most important information I should know about metformin hydrochloride tablets?”

What should I tell my healthcare provider before taking metformin hydrochloride tablets?

Before taking metformin hydrochloride Tablets, tell your healthcare provider if you:

- have type 1 diabetes. Metformin hydrochloride tablets should not be used to treat people with type 1 diabetes.
- have a history or risk for diabetic ketoacidosis (high levels of certain acids, known as ketones, in the blood or urine). Metformin hydrochloride tablets should not be used for the treatment of diabetic ketoacidosis.
- have kidney problems.
- have liver problems.
- have heart problems, including congestive heart failure.
- are older than 80 years. If you are over 80 years old you should not take metformin hydrochloride tablets unless your kidneys have been checked and they are normal.
- drink alcohol very often, or drink a lot of alcohol in short-term "binge"drinking.
- are taking insulin.
- have any other medical conditions.
- are pregnant or plan to become pregnant. It is not known if metformin hydrochloride tablets will harm your unborn baby. If you are pregnant, talk with your healthcare provider about the best way to control your blood sugar while you are pregnant.
- are breast-feeding or plan to breast-feed. It is not known if metformin hydrochloride tablets passes into your breast milk.Talk with your healthcare provider about the best way to feed your baby while you take metformin hydrochloride tablets.

Tell your healthcare provider about all the medicines you take, including prescription and nonprescription medicines, vitamins, and herbal supplements. Know the medicines you take. Keep a list of them to show your healthcare provider and pharmacist when you get a new medicine.

- Metformin hydrochloride tablets may affect the way other medicines work, and other medicines may affect how metformin hydrochloride tablets works.

Can metformin hydrochloride tablets be used in children?
Metformin hydrochloride tablets has been shown to effectively lower glucose levels in children (ages 10 to16 years) with type 2 diabetes. Metformin hydrochloride tablets has not been studied in children younger than 10 years old. Metformin hydrochloride tablets has not been studied in combination with other oral glucose-control medicines or insulin in children. If you have any questions about the use of metformin hydrochloride tablets in children, talk with your doctor or other healthcare provider.
How should I take metformin hydrochloride tablets?

- Take metformin hydrochloride tablets exactly as your healthcare provider tells you.
- Metformin hydrochloride tablets should be taken with meals to help lessen an upset stomach side effect.
- Swallow metformin hydrochloride tablets whole.
- You may sometimes pass a soft mass in your stools (bowel movement) that looks like metformin hydrochloride tablets. This is not harmful.
- When your body is under some types of stress, such as fever, trauma (such as a car accident), infection, or surgery, the amount of diabetes medicine that you need may change. Tell your healthcare provider right away if you have any of these problems.
- Your healthcare provider should do blood tests to check how well your kidneys are working before and during your treatment with metformin hydrochloride tablets .
- Your healthcare provider will check your diabetes with regular blood tests, including your blood sugar levels and your hemoglobin A1C.
- Follow your healthcare provider’s instructions for treating blood sugar that is too low (hypoglycemia). Talk to your healthcare provider if low blood sugar is a problem for you. See “ What are the possible side effects of metformin hydrochloride tablets?”
- Check your blood sugar as your healthcare provider tells you to.
- Stay on your prescribed diet and exercise program while taking metformin hydrochloride tablets.
- If you miss a dose of metformin hydrochloride tablets, take your next dose as prescribed unless your healthcare provider tells you differently. Do not take an extra dose the next day.
- If you take too much metformin hydrochloride tablets, call your healthcare provider, local Poison Control Center, or go to the nearest hospital emergency room right away

What should I avoid while taking metformin hydrochloride tablets?

Do not drink a lot of alcoholic drinks while taking metformin hydrochloride tablets. This means you should not binge drink for short periods, and you should not drink a lot of alcohol on a regular basis. Alcohol can increase the chance of getting lactic acidosis.

What are the side effects of metformin hydrochloride tablets?

- Lactic acidosis. Metformin, the active ingredient in metformin hydrochloride tablets, can cause a rare but serious condition called lactic acidosis (a buildup of an acid in the blood) that can cause death. Lactic acidosis is a medical emergency and must be treated in the hospital.

Call your doctor right away if you have any of the following symptoms, which could be signs of lactic acidosis:

- you feel cold in your hands or feet
- you feel dizzy or lightheaded
- you have a slow or irregular heartbeat
- you feel very weak or tired
- you have trouble breathing
- you feel sleepy or drowsy
- you have stomach pains, nausea or vomiting

Most people who have had lactic acidosis with metformin have other things that, combined with the metformin, led to the lactic acidosis. Tell your doctor if you have any of the following, because you have a higher chance for getting lactic acidosis with metformin hydrochloride tablets if you:

- have severe kidney problems, or your kidneys are affected by certain x-ray tests that use injectable dye

have liver problems

- drink alcohol very often, or drink a lot of alcohol in short-term "binge" drinking
- get dehydrated (lose a large amount of body fluids). This can happen if you are sick with a fever, vomiting, or diarrhea. Dehydration can also happen when you sweat a lot with activity or exercise and do not drink enough fluids
- have surgery
- have a heart attack, severe infection, or stroke

Common side effects of metformin hydrochloride tablets include diarrhea, nausea, and upset stomach. These side effects generally go away after you take the medicine for a while. Taking your medicine with meals can help reduce these side effects. Tell your doctor if the side effects bother you a lot, last for more than a few weeks, come back after they've gone away, or start later in therapy. You may need a lower dose or need to stop taking the medicine for a short period or for good.

About 3 out of every 100 people who take metformin hydrochloride tablets have an unpleasant metallic taste when they start taking the medicine. It lasts for a short time.

Metformin hydrochloride tablets rarely cause hypoglycemia (low blood sugar) by themselves. However, hypoglycemia can happen if you do not eat enough, if you drink alcohol, or if you take other medicines to lower blood sugar.

How should I store metformin hydrochloride tablets?

Store metformin hydrochloride tablets at 68ºF to 77ºF (20ºC to 25ºC).

Keep metformin hydrochloride tablets and all medicines out of the reach of children.

General information about the use of metformin hydrochloride tablets.

If you have questions or problems, talk with your doctor or other healthcare provider. You can ask your doctor or pharmacist for the information about metformin hydrochloride tablets that is written for healthcare professionals. Medicines are sometimes prescribed for purposes other than those listed in a patient information leaflet. Do not use metformin hydrochloride tablets for a condition for which it was not prescribed. Do not share your medicine with other people.
What are the ingredients of metformin hydrochloride tablets?

Active ingredients of Metformin hydrochloride tablets: metformin hydrochloride.
Inactive ingredients in each tablet of metformin hydrochloride tablets: Povidone (k-30), Povidone (k-90), pregelatinized starch, and magnesium stearate. In addition, the coating for the tablet contains artificial blackberry flavor, hypromellose, macrogol and titanium dioxide.

What is type 2 diabetes?

Type 2 diabetes is a condition in which your body does not make enough insulin, and the insulin that your body produces does not work as well as it should. Your body can also make too much sugar. When this happens, sugar (glucose) builds up in the blood. This can lead to serious medical problems.
The main goal of treating diabetes is to lower your blood sugar to a normal level.

High blood sugar can be lowered by diet and exercise, and by certain medicines when necessary.

Talk to your healthcare provider about how to prevent, recognize, and take care of low blood sugar (hypoglycemia), high blood sugar (hyperglycemia), and problems you have because of your diabetes.

Repackaged and Distributed By:

Remedy Repack, Inc.

625 Kolter Dr. Suite #4 Indiana, PA 1-724-465-8762

PACKAGE LABEL

DRUG: Metformin Hydrochloride

GENERIC: Metformin Hydrochloride

DOSAGE: TABLET

ADMINSTRATION: ORAL

NDC: 70518-3084-0

NDC: 70518-3084-1

NDC: 70518-3084-2

NDC: 70518-3084-3

NDC: 70518-3084-4

NDC: 70518-3084-5

NDC: 70518-3084-6

NDC: 70518-3084-7

COLOR: white

FLAVOR: BLACKBERRY

SHAPE: ROUND

SCORE: No score

SIZE: 13 mm

IMPRINT: G;11

PACKAGING: 30 in 1 BLISTER PACK

PACKAGING: 180 in 1 BOTTLE PLASTIC

PACKAGING: 90 in 1 BOTTLE PLASTIC

PACKAGING: 30 in 1 BLISTER PACK

PACKAGING: 90 in 1 BOTTLE PLASTIC

PACKAGING: 30 in 1 BLISTER PACK

PACKAGING: 180 in 1 BOTTLE PLASTIC

PACKAGING: 100 in 1 BOTTLE PLASTIC

ACTIVE INGREDIENT(S):

- METFORMIN HYDROCHLORIDE 850mg in 1

INACTIVE INGREDIENT(S):

- BLACKBERRY
- HYPROMELLOSE 2910 (6 MPA.S)
- POLYETHYLENE GLYCOL 400
- MAGNESIUM STEARATE
- POVIDONE K30
- POVIDONE K90
- STARCH, CORN
- TITANIUM DIOXIDE